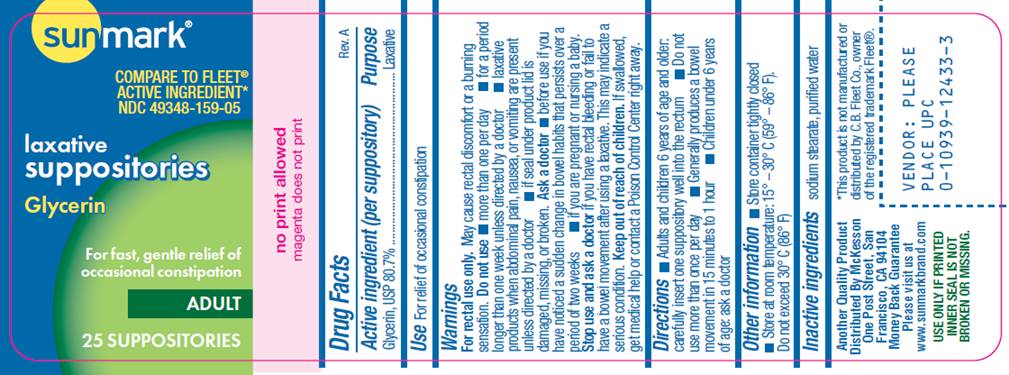 DRUG LABEL: Adult Glycerin Laxative
NDC: 49348-159 | Form: SUPPOSITORY
Manufacturer: McKesson
Category: otc | Type: HUMAN OTC DRUG LABEL
Date: 20100222

ACTIVE INGREDIENTS: glycerin 1.614 g/1 1
INACTIVE INGREDIENTS: sodium stearate; water

DRUG FACTS

ACTIVE INGREDIENT

Glycerin, USP 80.7%

PURPOSE

Laxative

USE

For relief of occasional constipation

WARNINGS

For rectal use only. May cause rectal discomfort or a burning sensation.

Do not use

- more than one per day
- for a period of longer than one week unless directed by a doctor
- laxative products when abdominal pain, nausea, or vominting are present unless directed by a doctor
- if seal under product lid is damaged, missing or broken.

Ask a doctor before use

- if you have noticed a sudden change in bowel habits that persist over a period of two weeks
- if you are pregnant or nursing a baby

Stop use and ask a doctor

if you have rectal bleeding or fail to have a bowel movement after using a laxative. This may indicate a serious condition.

Keep out of reach of children

If swallowed, get medical help or contact a Poison Control Center right away.

DIRECTIONS

- Adults and children 6 years of age and older: carefully insert one suppository well into the rectum
- Do not use more than once per day
- Generally produces a bowel movement in 15 minutes to 1 hour
- Children under 6 years of age: ask a doctor.

OTHER INFORMATION

- Store container tightly closed
- Store at room temperature: 15°- 30° C (59° - 86° F). Do not exceed 30° C (86° F).

INACTIVE INGREDIENTS

sodium stearate, purified water

PACKAGE LABEL - 25 count

sunmark®

COMPARE TO FLEET® ACTIVE INGREDIENT*
NDC 49348-159-05
Laxative
Suppositories
Glycerin

For fast, gentle relief of
occasional constipation
ADULT

25 SUPPOSITORIES

Another Quality Product
Distributed by McKesson
One Post Street, San
Francisco, CA 94104
Money Back Guarantee
Please visit us at
www.sunmarkbrand.com

USE ONLY IF PRINTED INNER SEAL IS NOT BROKEN OR MISSING
*This product is not manufactured or distributed by C.B. Fleet Co., owner of the registered trademark Fleet®.